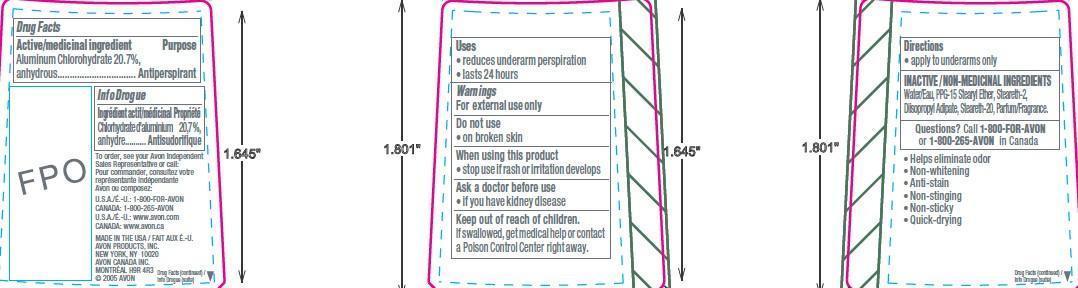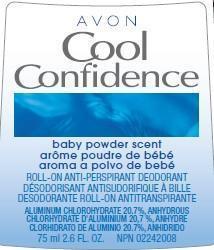 DRUG LABEL: Cool Confidence Baby Powder Scent
NDC: 10096-5214 | Form: GEL
Manufacturer: New Avon LLC
Category: otc | Type: HUMAN OTC DRUG LABEL
Date: 20190101

ACTIVE INGREDIENTS: ALUMINUM CHLOROHYDRATE	 207 mg/1 mL
INACTIVE INGREDIENTS: WATER

Cool Confidence Baby Powder Anti-Perspirant Roll-On Deodorant

Active ingredient

Aluminum Chlorohydrate 20.7%, anhydrous..

Purpose

..Antiperspirant

Uses

•reduces underarm perspiration

• lasts 24 hours

Warnings

For external use only

Do not use

- on broken skin

Ask a doctor before use if you have kidney disease

Stop use if rash or irritation occurs

Keep out of reach of children. If swallowed, get medical help or contact a poison control center right away.

When using this product
• stop use if rash or irritation develops

Ask a doctor before use
• if you have kidney disease

Keep out of reach of children.
If swallowed, get medical help or contact a Poison Control Center right away.

Directions

•apply to underarms only

Inactive ingredients

Water/Eau, PPG-15 Stearyl Ether, Steareth-2, Diisopropyl Adipate, Steareth-20, Parfum/Fragrance.

Questions?

Call 1-800-FOR-AVON or 1 -800-265-AVON in Canada